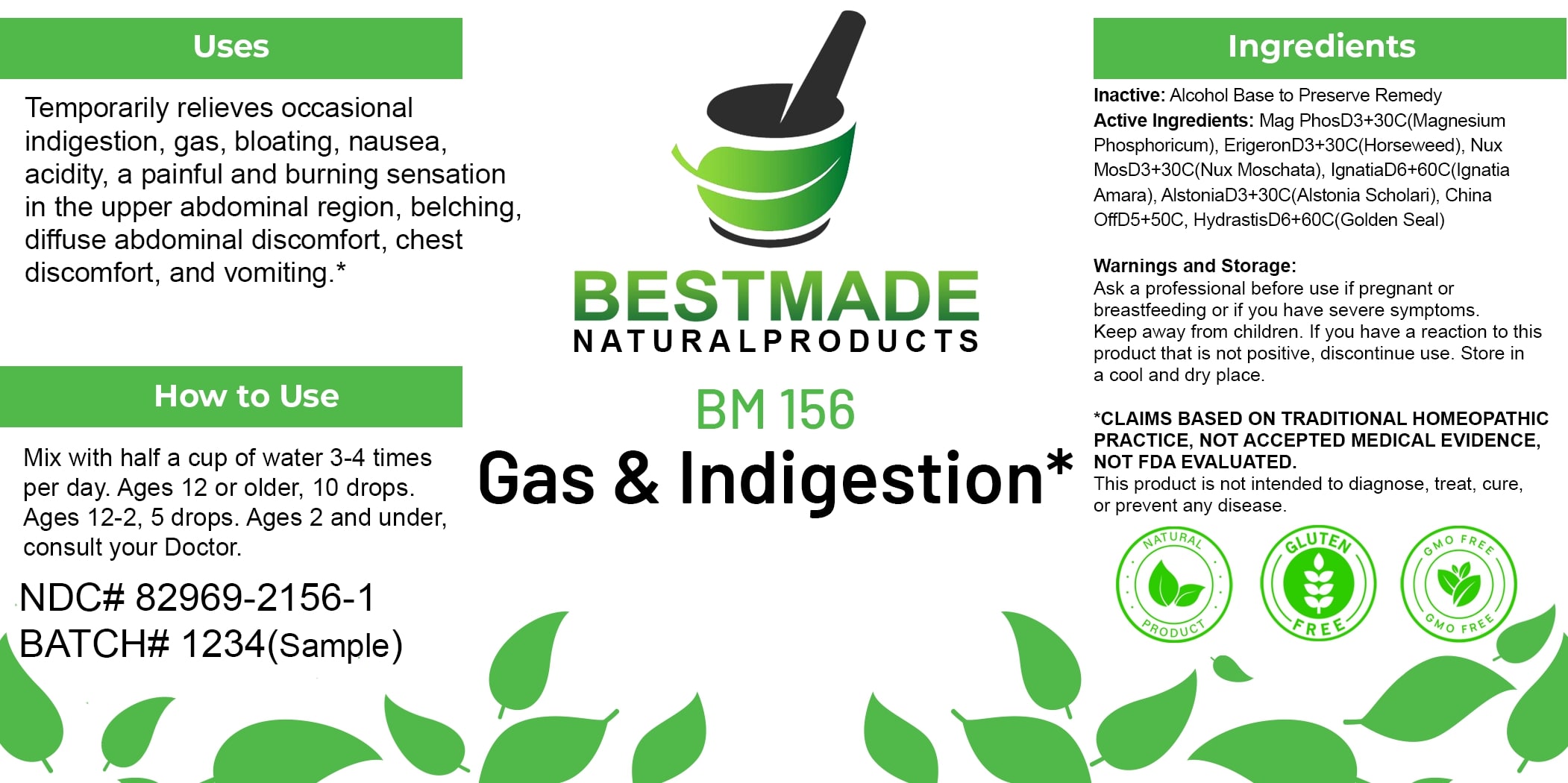 DRUG LABEL: Bestmade Natural Products BM156
NDC: 82969-2156 | Form: LIQUID
Manufacturer: Bestmade Natural Products
Category: homeopathic | Type: HUMAN OTC DRUG LABEL
Date: 20250218

ACTIVE INGREDIENTS: ALSTONIA SCHOLARIS BARK 30 [hp_C]/30 [hp_C]; GOLDENSEAL 30 [hp_C]/30 [hp_C]; MAGNESIUM PHOSPHATE, DIBASIC TRIHYDRATE 30 [hp_C]/30 [hp_C]; NUTMEG 30 [hp_C]/30 [hp_C]; CINCHONA OFFICINALIS BARK 30 [hp_C]/30 [hp_C]; ERIGERON CANADENSIS 30 [hp_C]/30 [hp_C]; STRYCHNOS IGNATII SEED 30 [hp_C]/30 [hp_C]
INACTIVE INGREDIENTS: ALCOHOL 30 [hp_C]/30 [hp_C]

BM156

DOSAGE AND ADMINISTRATION

How to Use

Mix with half a cup of water 3-4 times per day. Ages 12 or older, 10 drops. Ages 12-2, 5 drops. Ages 2 and under, consult your Doctor.

INACTIVE INGREDIENT

Ingredients

Inactive: Alcohol Base to Preserve Remedy

ACTIVE INGREDIENT

Active Ingredients: Mag PhosD3+30C(Magnesium Phosphoricum), ErigeronD3+30C(Horseweed), Nux MosD3+30C(Nux Moschata), IgnatiaD6+60C(Ignatia Amara), AlstoniaD3+30C(Alstonia Scholaris), China OffD5+50C, HydrastisD6+60C(Golden Seal)

Uses

Temporarily relieves occasional indigestion, gas, bloating, nausea, acidity, a painful and burning sensation in the upper abdominal region, belching, diffuse abdominal discomfort, chest discomfort, and vomiting.*

*CLAIMS BASED ON TRADITIONAL HOMEOPATHIC PRACTICE, NOT ACCEPTED MEDICAL EVIDENCE. NOT FDA EVALUATED.

This product is not intended to diagnose, treat, cure, or prevent any disease.

KEEP OUT OF REACH OF CHILDREN

Warnings and Storage:

Ask a professional before use if pregnant or breastfeeding or if you have severe symptoms. Keep away from children. If you have a reaction to this product that is not positive, discontinue use. Store in a cool and dry place.

Uses

Temporarily relieves occasional indigestion, gas, bloating, nausea, acidity, a painful and burning sensation in the upper abdominal region, belching, diffuse abdominal discomfort, chest discomfort, and vomiting.*

*CLAIMS BASED ON TRADITIONAL HOMEOPATHIC PRACTICE, NOT ACCEPTED MEDICAL EVIDENCE. NOT FDA EVALUATED.

This product is not intended to diagnose, treat, cure, or prevent any disease.

Warnings and Storage:

Ask a professional before use if pregnant or breastfeeding or if you have severe symptoms. Keep away from children. If you have a reaction to this product that is not positive, discontinue use. Store in a cool and dry place.

*CLAIMS BASED ON TRADITIONAL HOMEOPATHIC PRACTICE, NOT ACCEPTED MEDICAL EVIDENCE. NOT FDA EVALUATED.

This product is not intended to diagnose, treat, cure, or prevent any disease.

Entire package label